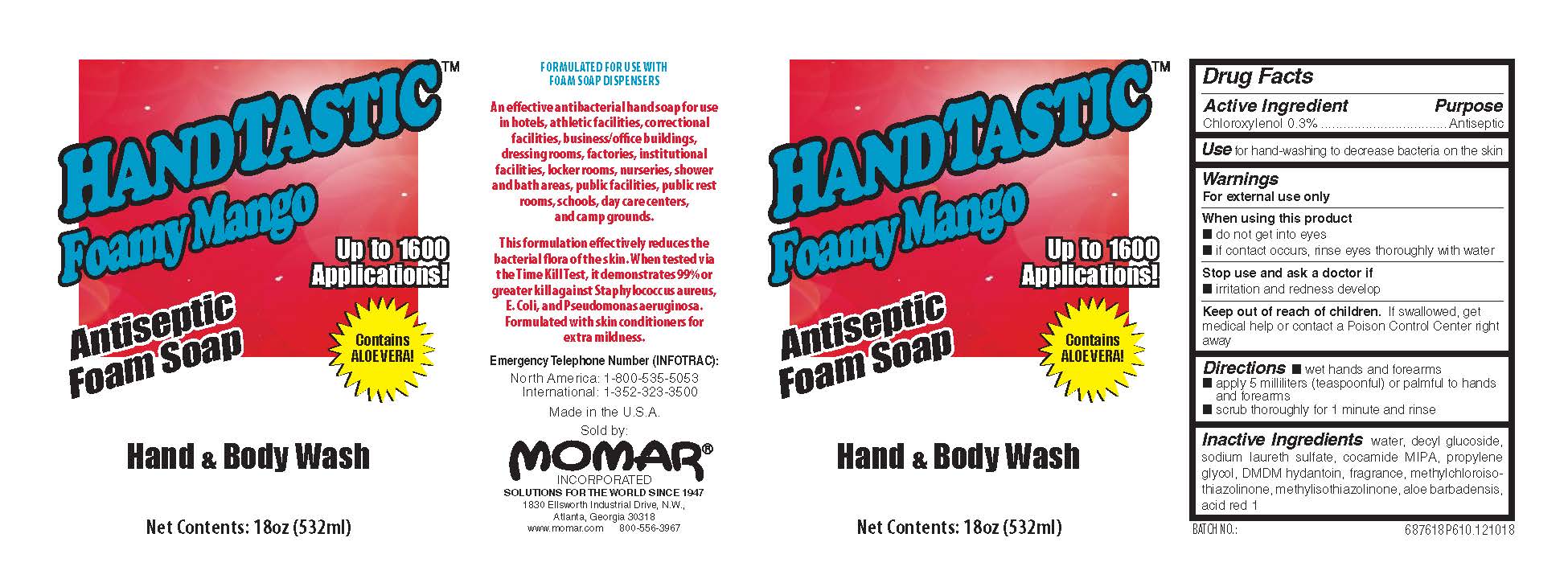 DRUG LABEL: Handtastic Foamy Mango Antiseptic Hand and Body Wash
NDC: 63533-876 | Form: SOAP
Manufacturer: Momar Incorporated
Category: otc | Type: HUMAN OTC DRUG LABEL
Date: 20260105

ACTIVE INGREDIENTS: CHLOROXYLENOL 3 mg/1 mL
INACTIVE INGREDIENTS: WATER; PROPYLENE GLYCOL; SODIUM LAURETH SULFATE; DECYL GLUCOSIDE; ACID RED 1; METHYLCHLOROISOTHIAZOLINONE; METHYLISOTHIAZOLINONE; DMDM HYDANTOIN; ALOE VERA LEAF

Handtastic Foamy Mango Antiseptic Hand and Body Wash 6876 Drug facts and Label

Drug Facts Box OTC-Active Ingredient Section

Chloroxylenol 0.3%

Drug Facts Box OTC-Purpose Section

Antiseptic

Drug Facts Box OTC-Indications & Usage Section

for hand-washing to decrease bacteria on the skin

Drug Facts Box OTC-Warnings Section

For external use only

Drug Facts Box OTC-When Using Section

do not get into eyes

if contact occurs, rinse eyes thoroughly with water

Drug Facts Box OTC-Stop Use Section

irritation and redness develop

Drug Facts Box OTC-Keep Out of Reach of Children Section

if swallowed, get medical help or contact a Poison Control Center right away

Drug Facts Box OTC-Dosage & Administration Section

- wet hands and forearms
- apply 5 milliliters (teaspoonful) or palmful to hands and forearms
- scrub thoroughly for 1 minute and rinse

Drug Facts Box OTC-Inactive Ingredient Section

water, decyl glucoside, sodium laureth sulfate, cocamide MIPA, propylene glycol, DMDM hydantoin, fragrance, methylchloroisothiazolinone, methylisothiazolinone, aloe barbadensis, acid red 1

Handtastic Foamy Mango Antiseptic Hand and Body Wash 6876 Label